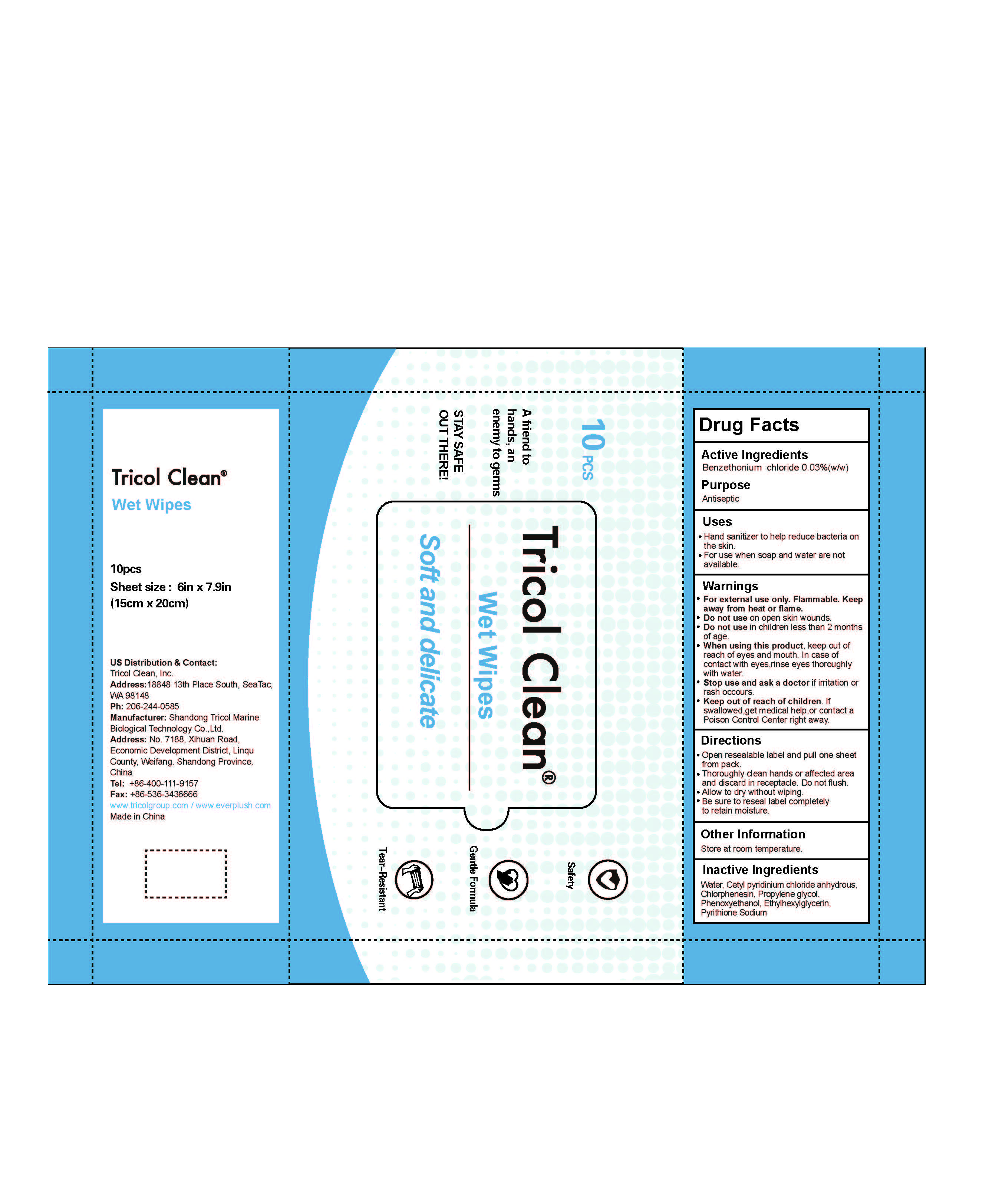 DRUG LABEL: wet wipes
NDC: 54156-002 | Form: CLOTH
Manufacturer: Shandong Tricol Marine Biological Technology Co.,Ltd
Category: otc | Type: HUMAN OTC DRUG LABEL
Date: 20210129

ACTIVE INGREDIENTS: BENZETHONIUM CHLORIDE 0.03 g/100 g
INACTIVE INGREDIENTS: PROPYLENE GLYCOL; ETHYLHEXYLGLYCERIN; PYRITHIONE SODIUM; CHLORPHENESIN; WATER; PHENOXYETHANOL; CETYLPYRIDINIUM CHLORIDE ANHYDROUS

Active Ingredient(s)

Benzethonium chloride 0.03% （w/w）

Purpose

Antiseptic

Use

to help reduce bacteria on the skin.

for use when soap and water are not available.

Warnings

For external use only. Flammable. Keep away from heat or flame

Do not use

- in children less than 2 months of age
- on open skin wounds

When using this product keep out of eyes, ears, and mouth. In case of contact with eyes, rinse eyes thoroughly with water.
Stop use and ask a doctor if irritation or rash occurs. These may be signs of a serious condition.
Keep out of reach of children. If swallowed, get medical help or contact a Poison Control Center right away.

Stop use and ask a doctor if irritation or rash occurs. These may be signs of a serious condition.

Keep out of reach of children. If swallowed, get medical help or contact a Poison Control Center right away.

Directions

Tear the packaging at the zigzag edge to use

Other information

- Store at room temperature

Inactive ingredients

Water,Cetylpyridinium chloride anhydrous,Chlorphenesin,Propylene glycol,Phenoxyethanol,Ethylhexylglycerin,Phrithione Sodium